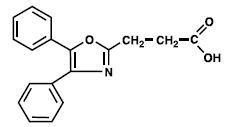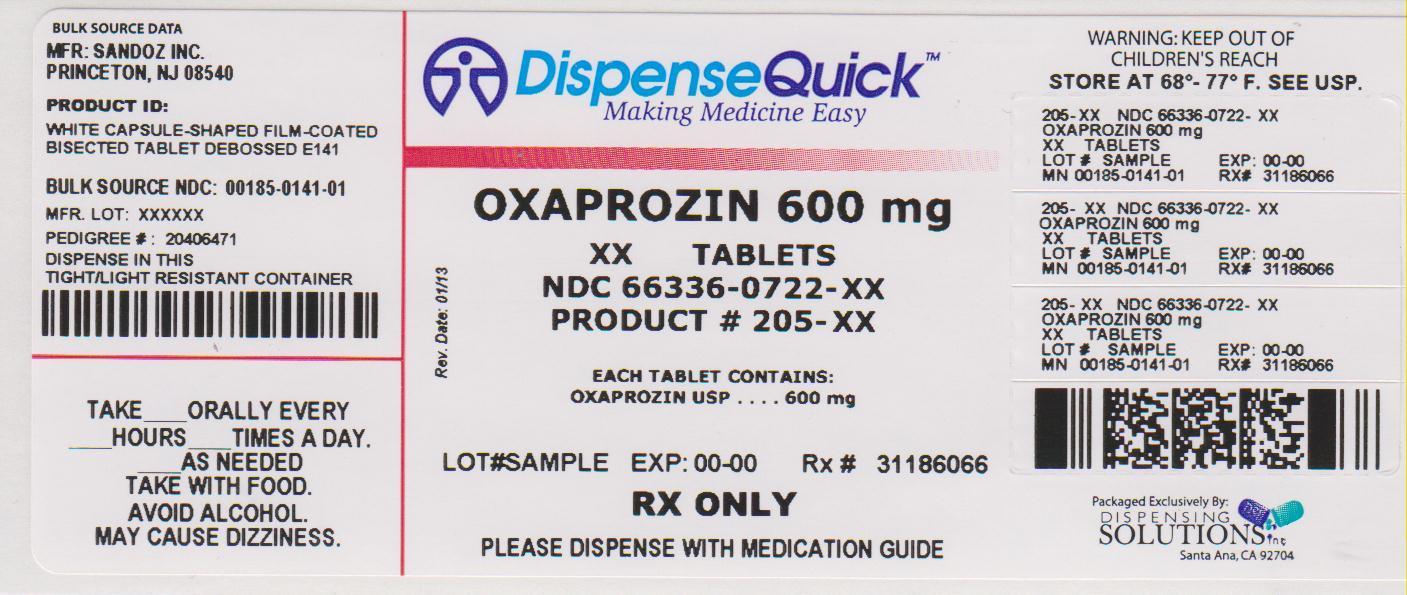 DRUG LABEL: Oxaprozin
NDC: 66336-722 | Form: TABLET
Manufacturer: Dispensing Solutions, Inc.
Category: prescription | Type: HUMAN PRESCRIPTION DRUG LABEL
Date: 20130703

ACTIVE INGREDIENTS: OXAPROZIN 600 mg/1 1
INACTIVE INGREDIENTS: SILICON DIOXIDE; HYPROMELLOSES; MAGNESIUM STEARATE; METHYLCELLULOSE (100 CPS); CELLULOSE, MICROCRYSTALLINE; POLACRILIN POTASSIUM; POLYETHYLENE GLYCOLS; POLYSORBATE 80; STARCH, CORN; TITANIUM DIOXIDE

Oxaprozin Tablets USP

BOXED WARNING

Cardiovascular Risk

- NSAIDs may cause an increased risk of serious cardiovascular thrombotic events, myocardial infarction, and stroke, which can be fatal. This risk may increase with duration of use. Patients with cardiovascular disease or risk factors for cardiovascular disease may be at greater risk. (See WARNINGS).

- Oxaprozin is contraindicated for treatment of peri-operative pain in the setting of coronary artery bypass graft (CABG) surgery (see WARNINGS).

Gastrointestinal Risk

- NSAIDs cause an increased risk of serious gastrointestinal adverse events including bleeding, ulceration, and perforation of the stomach or intestines, which can be fatal. These events can occur at any time during use and without warning symptoms. Elderly patients are at greater risk for serious gastrointestinal events. (See WARNINGS).

DESCRIPTION

Oxaprozin USP is a nonsteroidal anti-inflammatory drug (NSAID), chemically designated as 4,5-diphenyl-2-oxazole-propionic acid, and has the following chemical structure:

The empirical formula for oxaprozin USP is C18H15NO3, and the molecular weight is 293. Oxaprozin USP is a white to off-white powder with a slight odor and a melting point of 162°C to 163°C. It is slightly soluble in alcohol and insoluble in water, with an octanol/water partition coefficient of 4.8 at physiologic pH (7.4). The pKa in water is 4.3.

Oxaprozin tablets USP contain 600 mg of oxaprozin USP.

In addition, each tablet of oxaprozin USP contains the following inactive ingredients: colloidal silicon dioxide, microcrystalline cellulose, hypromellose, methylcellulose, magnesium stearate, polacrilin potassium, starch, polyethylene glycol, titanium dioxide, and polysorbate 80.

CLINICAL PHARMACOLOGY

Pharmacodynamics

Oxaprozin is a nonsteroidal anti-inflammatory drug (NSAID) that exhibits anti-inflammatory, analgesic, and antipyretic properties in animal models. The mechanism of action of oxaprozin, like that of other NSAIDs, is not completely understood but may be related to prostaglandin synthetase inhibition.

Pharmacokinetics (see Table 1 Oxaprozin Pharmacokinetic Parameters [Mean (%CV)] (1200 mg))

Absorption

Oxaprozin is 95% absorbed after oral administration. Food may reduce the rate of absorption of oxaprozin, but the extent of absorption is unchanged. Antacids do not significantly affect the extent and rate of oxaprozin absorption.

Table 1 Oxaprozin Pharmacokinetic Parameters [Mean (%CV)] (1200 mg)
 | Healthy Adults (19-78 years)
 | Total Drug |  | Unbound Drug
 | Single; N=35 | Multiple; N=12 | Single; N=35 | Multiple; N=12
Tmax (hr) | 3.09 (39) | 2.44 (40) | 3.03 (48) | 2.33 (35)
Oral Clearance (L/hr/70 kg) | 0.150 (24) | 0.301 (29) | 136 (24) | 102 (45)
Apparent Volume of Distribution at; Steady State (Vd/F; L/70 kg) | 11.7 (13) | 16.7 (14) | 6230 (28) | 2420 (38)
Elimination Half-life (hr) | 54.9 (49) | 41.4 (27) | 27.8 (34) | 19.5 (15)

Distribution

In dose proportionality studies utilizing 600 mg, 1200 mg and 1800 mg doses, the pharmacokinetics of oxaprozin in healthy subjects demonstrated non-linear kinetics of both the total and unbound drug in opposite directions, i.e., dose exposure related increase in the clearance of total drug and decrease in the clearance of the unbound drug. Decreased clearance of the unbound drug was related predominantly to a decrease in the volume of distribution and not an increase in the half-life. This phenomenon is considered to have minimal impact on drug accumulation upon multiple dosing.

The apparent volume of distribution (Vd/F) of total oxaprozin is approximately 11 L/70 kg to 17 L/70 kg. Oxaprozin is 99% bound to plasma proteins, primarily to albumin. At therapeutic drug concentrations, the plasma protein binding of oxaprozin is saturable, resulting in a higher proportion of the free drug as the total drug concentration is increased. With increases in single doses or following repetitive once-daily dosing, the apparent volume of distribution and clearance of total drug increased, while that of unbound drug decreased due to the effects of non-linear protein binding. Oxaprozin penetrates into synovial tissues of rheumatoid arthritis patients with oxaprozin concentrations 2-fold and 3-fold greater than in plasma and synovial fluid, respectively. Oxaprozin is expected to be excreted in human milk based on its physical-chemical properties; however, the amount of oxaprozin excreted in breast milk has not been evaluated.

Metabolism

Several oxaprozin metabolites have been identified in human urine or feces. Oxaprozin is primarily metabolized by the liver, by both microsomal oxidation (65%) and glucuronic acid conjugation (35%). Ester and ether glucuronide are the major conjugated metabolites of oxaprozin. On chronic dosing, metabolites do not accumulate in the plasma of patients with normal renal function. Concentrations of the metabolites in plasma are very low.

Oxaprozin’s metabolites do not have significant pharmacologic activity. The major ester and ether glucuronide conjugated metabolites have been evaluated along with oxaprozin in receptor binding studies and in vivo animal models and have demonstrated no activity. A small amount (<5%) of active phenolic metabolites are produced, but the contribution to overall activity is limited.

Excretion

Approximately 5% of the oxaprozin dose is excreted unchanged in the urine. Sixty-five percent (65%) of the dose is excreted in the urine and 35% in the feces as metabolite. Biliary excretion of unchanged oxaprozin is a minor pathway, and enterohepatic recycling of oxaprozin is insignificant. Upon chronic dosing the accumulation half-life is approximately 22 hours. The elimination half-life is approximately twice the accumulation half-life due to increased binding and decreased clearance at lower concentrations.

Special Populations

Pediatric Patients

A population pharmacokinetic study indicated no clinically important age dependent changes in the apparent clearance of unbound oxaprozin between adult rheumatoid arthritis patients (N=40) and juvenile rheumatoid arthritis (JRA) patients (≥6 years, N=44) when adjustments were made for differences in body weight between these patient groups. The extent of protein binding of oxaprozin at various therapeutic total plasma concentrations was also similar between the adult and pediatric patient groups. Pharmacokinetic model-based estimates of daily exposure (AUC0-24) to unbound oxaprozin in JRA patients relative to adult rheumatoid arthritis patients suggest dose to body weight range relationships as shown in Table 2. No pharmacokinetic data are available for pediatric patients under 6 years of age (see PRECAUTIONS, Pediatric Use).

Table 2 Dose to body weight range to achieve similar steady-state exposure (AUC0-24hr) to unbound oxaprozin in JRA patients relative to 70 kg adult rheumatoid arthritis patients administered oxaprozin 1200 mg QD [Model-based nomogram derived from unbound oxaprozin steady-state drug plasma concentrations of JRA patients weighing 22.1 kg to 42.7 kg or ≥45.0 kg administered oxaprozin 600 mg or 1200 mg QD for 14 days, respectively.]
Dose (mg) | Body Weight Range; (kg)
600 | 22 - 31
900 | 32 - 54
1200 | ≥ 55

Geriatric Patients

As with any NSAID, caution should be exercised in treating the elderly (65 years and older). No dosage adjustment is necessary in the elderly for pharmacokinetics reasons, although many elderly may need a reduced dose due to low body weight or disorders associated with aging.

A multiple dose study comparing the pharmacokinetics of oxaprozin (1200 mg QD) in 20 young (21 to 44 years) adults and 20 elderly (64 to 83 years) adults, did not show any statistically significant differences between age groups.

Race

Pharmacokinetics differences due to race have not been identified.

Hepatic Insufficiency

Approximately 95% of oxaprozin is metabolized by the liver. However, patients with well compensated cirrhosis do not require reduced doses of oxaprozin as compared to patients with normal hepatic function. Nevertheless, caution should be observed in patients with severe hepatic dysfunction.

Cardiac Failure

Well-compensated cardiac failure does not affect the plasma protein binding or the pharmacokinetics of oxaprozin.

Renal Insufficiency

The pharmacokinetics of oxaprozin have been investigated in patients with renal insufficiency. Oxaprozin’s renal clearance decreased proportionally with creatinine clearance (CrCl), but since only about 5% of oxaprozin dose is excreted unchanged in the urine, the decrease in total body clearance becomes clinically important only in those subjects with highly decreased CrCl. Oxaprozin is not significantly removed from the blood in patients undergoing hemodialysis or continuous ambulatory peritoneal dialysis (CAPD) due to its high protein binding. Oxaprozin plasma protein binding may decrease in patients with severe renal deficiency. Dosage adjustment may be necessary in patients with renal insufficiency (see WARNINGS, Renal Effects).

CLINICAL STUDIES

Rheumatoid Arthritis

Oxaprozin was evaluated for managing the signs and symptoms of rheumatoid arthritis in placebo and active controlled clinical trials in a total of 646 patients. Oxaprozin was given in single or divided daily doses of 600 mg/day to 1800 mg/day and was found to be comparable to 2600 mg/day to 3900 mg/day of aspirin. At these doses there was a trend (over all trials) for oxaprozin to be more effective and cause fewer gastrointestinal side effects than aspirin.

Oxaprozin was given as a once-a-day dose of 1200 mg in most of the clinical trials, but larger doses (up to 26 mg/kg or 1800 mg/day) were used in selected patients. In some patients, oxaprozin may be better tolerated in divided doses. Due to its long half-life, several days of oxaprozin therapy were needed for the drug to reach its full effect (see DOSAGE AND ADMINISTRATION, Individualization of Dosage).

Osteoarthritis

Oxaprozin was evaluated for the management of the signs and symptoms of osteoarthritis in a total of 616 patients in active controlled clinical trials against aspirin (N=464), piroxicam (N=102), and other NSAIDs. Oxaprozin was given both in variable (600 mg/day to 1200 mg/day) and in fixed (1200 mg/day) dosing schedules in either single or divided doses. In these trials, oxaprozin was found to be comparable to 2600 mg/day to 3200 mg/day doses of aspirin or 20 mg/day doses of piroxicam. Oxaprozin was effective both in once daily and in divided dosing schedules. In controlled clinical trials several days of oxaprozin therapy were needed for the drug to reach its full effects (see DOSAGE AND ADMINISTRATION, Individualization of Dosage).

INDICATIONS AND USAGE

Carefully consider the potential benefits and risks of oxaprozin tablets USP and other treatment options before deciding to use oxaprozin tablets USP. Use the lowest effective dose for the shortest duration consistent with individual patient treatment goals (see WARNINGS).

Oxaprozin tablets USP are indicated:

- For relief of the signs and symptoms of osteoarthritis.
- For relief of the signs and symptoms of rheumatoid arthritis.
- For relief of the signs and symptoms of juvenile rheumatoid arthritis.

CONTRAINDICATIONS

Oxaprozin is contraindicated in patients with known hypersensitivity to oxaprozin.

Oxaprozin should not be given to patients who have experienced asthma, urticaria, or allergic-type reactions after taking aspirin or other NSAIDs. Severe, rarely fatal, anaphylactic-like reactions to NSAIDs have been reported in such patients (see WARNINGS, Anaphylactoid Reactionsand PRECAUTIONS, Pre-existing Asthma).

Oxaprozin is contraindicated for the treatment of peri-operative pain in the setting of coronary artery bypass graft (CABG) surgery (see WARNINGS).

WARNINGS

Cardiovascular Effects

Cardiovascular Thrombotic Events

Clinical trials of several COX-2 selective and nonselective NSAIDs of up to three years duration have shown an increased risk of serious cardiovascular (CV) thrombotic events, myocardial infarction, and stroke, which can be fatal. All NSAIDs, both COX-2 selective and nonselective, may have a similar risk. Patients with known CV disease or risk factors for CV disease may be at greater risk. To minimize the potential risk for an adverse CV event in patients treated with an NSAID, the lowest effective dose should be used for the shortest duration possible. Physicians and patients should remain alert for the development of such events, even in the absence of previous CV symptoms. Patients should be informed about the signs and/or symptoms of serious CV events and the steps to take if they occur.

There is no consistent evidence that concurrent use of aspirin mitigates the increased risk of serious CV thrombotic events associated with NSAID use. The concurrent use of aspirin and an NSAID does increase the risk of serious GI events (see WARNINGS, Gastrointestinal Effects - Risk of Ulceration, Bleeding, and Perforation).

Two large, controlled clinical trials of a COX-2 selective NSAID for the treatment of pain in the first 10 to 14 days following CABG surgery found an increased incidence of myocardial infarction and stroke (see CONTRAINDICATIONS).

Hypertension

NSAIDs, including oxaprozin, can lead to onset of new hypertension or worsening of pre-existing hypertension, either of which may contribute to the increased incidence of CV events. Patients taking thiazides or loop diuretics may have impaired response to these therapies when taking NSAIDs. NSAIDs, including oxaprozin, should be used with caution in patients with hypertension. Blood pressure (BP) should be monitored closely during the initiation of NSAID treatment and throughout the course of therapy.

Congestive Heart Failure and Edema

Fluid retention and edema have been observed in some patients taking NSAIDs. Oxaprozin should be used with caution in patients with fluid retention or heart failure.

Gastrointestinal Effects - Risk of Ulceration, Bleeding, and Perforation

NSAIDs, including oxaprozin, can cause serious gastrointestinal (GI) adverse events including inflammation, bleeding, ulceration, and perforation of the stomach, small intestine, or large intestine, which can be fatal. These serious adverse events can occur at any time, with or without warning symptoms, in patients treated with NSAIDs. Only one in five patients, who develop a serious upper GI adverse event on NSAID therapy, is symptomatic. Upper GI ulcers, gross bleeding, or perforation caused by NSAIDs occur in approximately 1% of patients treated for 3 to 6 months, and in about 2% to 4% of patients treated for one year. These trends continue with longer duration of use, increasing the likelihood of developing a serious GI event at some time during the course of therapy. However, even short-term therapy is not without risk.

NSAIDs should be prescribed with extreme caution in those with a prior history of ulcer disease or gastrointestinal bleeding. Patients with a prior history of peptic ulcer disease and/or gastrointestinal bleeding who use NSAIDs have a greater than 10-fold increased risk for developing a GI bleed compared to patients treated with neither of these risk factors. Other factors that increase the risk of GI bleeding in patients treated with NSAIDs include concomitant use of oral corticosteroids or anticoagulants, longer duration of NSAID therapy, smoking, use of alcohol, older age, and poor general health status. Most spontaneous reports of fatal GI events are in elderly or debilitated patients and therefore, special care should be taken in treating this population.

To minimize the potential risk for an adverse GI event in patients treated with an NSAID, the lowest effective dose should be used for the shortest possible duration. Patients and physicians should remain alert for signs and symptoms of GI ulcerations and bleeding during NSAID therapy and promptly initiate additional evaluation and treatment if a serious GI event is suspected. This should include discontinuation of the NSAID until a serious GI adverse event is ruled out. For high risk patients, alternate therapies that do not involve NSAIDs should be considered.

Renal Effects

Long-term administration of NSAIDs has resulted in renal papillary necrosis and other renal injury. Renal toxicity has also been seen in patients in whom renal prostaglandins have a compensatory role in the maintenance of renal perfusion. In these patients, administration of a nonsteroidal anti-inflammatory drug may cause a dose dependent reduction in prostaglandin formation and, secondarily, in renal blood flow, which may precipitate overt renal decompensation. Patients at greatest risk of this reaction are those with impaired renal function, heart failure, liver dysfunction, those taking diuretics and ACE inhibitors, and the elderly. Discontinuation of NSAID therapy is usually followed by recovery to the pretreatment state.

Advanced Renal Disease

No information is available from controlled clinical studies regarding the use of oxaprozin in patients with advanced renal disease. Therefore, treatment with oxaprozin is not recommended in these patients with advanced renal disease. If oxaprozin therapy must be initiated, close monitoring of the patient's renal function is advisable.

Anaphylactoid Reactions

As with other NSAIDs, anaphylactoid reactions may occur in patients without known prior exposure to oxaprozin. Oxaprozin should not be given to patients with the aspirin triad. This symptom complex typically occurs in asthmatic patients who experience rhinitis with or without nasal polyps, or who exhibit severe, potentially fatal bronchospasm after taking aspirin or other NSAIDs (see CONTRAINDICATIONS and PRECAUTIONS, Pre-existing Asthma). Emergency help should be sought in cases where an anaphylactoid reaction occurs.

Skin Reactions

NSAIDs, including oxaprozin, can cause serious skin adverse events such as exfoliative dermatitis, Stevens-Johnson Syndrome (SJS), and toxic epidermal necrolysis (TEN), which can be fatal. These serious events may occur without warning. Patients should be informed about the signs and symptoms of serious skin manifestations and use of the drug should be discontinued at the first appearance of skin rash or any other sign of hypersensitivity.

Pregnancy

In late pregnancy, as with other NSAIDs, oxaprozin should be avoided because it may cause premature closure of the ductus arteriosus.

PRECAUTIONS

General

Oxaprozin cannot be expected to substitute for corticosteroids or to treat corticosteroid insufficiency. Abrupt discontinuation of corticosteroids may lead to disease exacerbation. Patients on prolonged corticosteroid therapy should have their therapy tapered slowly if a decision is made to discontinue corticosteroids.

The pharmacological activity of oxaprozin in reducing fever and inflammation may diminish the utility of these diagnostic signs in detecting complications of presumed noninfectious, painful conditions.

Hepatic Effects

Borderline elevations of one or more liver tests may occur in up to 15% of patients taking NSAIDs including oxaprozin. These laboratory abnormalities may progress, may remain unchanged, or may be transient with continued therapy. Notable elevations of ALT or AST (approximately three or more times the upper limit of normal) have been reported in approximately 1% of patients in clinical trials with NSAIDs. In addition, rare cases of severe hepatic reactions, including jaundice and fatal fulminant hepatitis, liver necrosis and hepatic failure, some of them with fatal outcomes have been reported.

A patient with symptoms and/or signs suggesting liver dysfunction, or in whom an abnormal liver test has occurred, should be evaluated for evidence of the development of a more severe hepatic reaction while on therapy with oxaprozin. If clinical signs and symptoms consistent with liver disease develop, or if systemic manifestations occur (e.g., eosinophilia, rash, etc.), oxaprozin should be discontinued.

Photosensitivity

Oxaprozin has been associated with rash and/or mild photosensitivity in dermatologic testing. An increased incidence of rash on sun-exposed skin was seen in some patients in the clinical trials.

Hematological Effects

Anemia is sometimes seen in patients receiving NSAIDs, including oxaprozin. This may be due to fluid retention, occult or gross GI blood loss, or an incompletely described effect upon erythrogenesis. Patients on long-term treatment with oxaprozin should have their hemoglobin or hematocrit values determined if they exhibit any signs or symptoms of anemia.

NSAIDs inhibit platelet aggregation and have been shown to prolong bleeding time in some patients. Unlike aspirin, their effect on platelet function is quantitatively less, of shorter duration, and reversible. Patients receiving oxaprozin who may be adversely affected by alterations in platelet function, such as those with coagulation disorders or patients receiving anticoagulants, should be carefully monitored.

Pre-existing Asthma

Patients with asthma may have aspirin-sensitive asthma. The use of aspirin in patients with aspirin-sensitive asthma has been associated with the severe bronchospasm which can be fatal. Since cross reactivity, including bronchospasm, between aspirin and other nonsteroidal anti-inflammatory drugs has been reported in such aspirin-sensitive patients, oxaprozin should not be administered to patients with this form of aspirin sensitivity and should be used with caution in patients with pre-existing asthma.

Information for Patients

Patients should be informed of the following information before initiating therapy with an NSAID and periodically during the course of ongoing therapy. Patients should also be encouraged to read the NSAID Medication Guide that accompanies each prescription dispensed.

1. Oxaprozin, like other NSAIDs, may cause CV side effects, such as MI or stroke, which may result in hospitalization and even death. Although serious CV events can occur without warning symptoms, patients should be alert for the signs and symptoms of chest pain, shortness of breath, weakness, slurring of speech, and should ask for medical advice when observing any indicative sign or symptoms. Patients should be apprised of the importance of this follow-up (see WARNINGS, Cardiovascular Effects).
2. Oxaprozin, like other NSAIDs, can cause GI discomfort and, rarely, serious GI side effects, such as ulcers and bleeding, which may result in hospitalization and even death. Although serious GI tract ulcerations and bleeding can occur without warning symptoms, patients should be alert for the signs and symptoms of ulcerations and bleeding, and should ask for medical advice when observing any indicative sign or symptoms including epigastric pain, dyspepsia, melena, and hematemesis. Patients should be apprised of the importance of this follow-up (see WARNINGS, Gastrointestinal Effects - Risk of Ulceration, Bleeding, and Perforation).
3. Oxaprozin, like other NSAIDs, can cause serious skin side effects such as exfoliative dermatitis, SJS and TEN, which may result in hospitalization and even death. Although serious skin reactions may occur without warning, patients should be alert for the signs and symptoms of skin rash and blisters, fever, or other signs of hypersensitivity such as itching, and should ask for medical advice when observing any indicative signs or symptoms. Patients should be advised to stop the drug immediately if they develop any type of rash and contact their physicians as soon as possible.
4. Patients should promptly report signs or symptoms of unexplained weight gain or edema to their physicians.
5. Patients should be informed of the warning signs and symptoms of hepatotoxicity (e.g., nausea, fatigue, lethargy, pruritus, jaundice, right upper quadrant tenderness and "flu-like" symptoms). If these occur, patients should be instructed to stop therapy and seek immediate medical therapy.
6. Patients should be informed of the signs of an anaphylactoid reaction (e.g. difficulty breathing, swelling of the face or throat). If these occur, patients should be instructed to seek immediate emergency help (see WARNINGS, Anaphylactoid ReactionsAnaphylactoid).
7. In late pregnancy, as with other NSAIDs, oxaprozin should be avoided because it may cause premature closure of the ductus arteriosus.

Laboratory Tests

Because serious GI tract ulcerations and bleeding can occur without warning symptoms, physicians should monitor for signs or symptoms of GI bleeding. Patients on long-term treatment with NSAIDs, should have their CBC and a chemistry profile checked periodically. If clinical signs and symptoms consistent with liver or renal disease develop, systemic manifestations occur (e.g., eosinophilia, rash, etc.) or if abnormal liver tests persist or worsen, oxaprozin should be discontinued.

Drug Interactions

Aspirin

Concomitant administration of oxaprozin and aspirin is not recommended because oxaprozin displaces salicylates from plasma protein binding sites. Co-administration would be expected to increase the risk of salicylate toxicity. As with other NSAIDs, concomitant administration of oxaprozin and aspirin is not generally recommended because of the potential for increased adverse effects.

Methotrexate

NSAIDs have been reported to competitively inhibit methotrexate accumulation in rabbit kidney slices. This may indicate that they could enhance the toxicity of methotrexate. Caution should be used when NSAIDs are administered concomitantly with methotrexate. Co-administration of oxaprozin with methotrexate results in approximately a 36% reduction in apparent oral clearance of methotrexate. A reduction in methotrexate dosage may be considered due to the potential for increased methotrexate toxicity associated with the increased exposure.

ACE-inhibitors

Reports suggest that NSAIDs may diminish the antihypertensive effect of ACE-inhibitors. Oxaprozin has been shown to alter the pharmacokinetics of enalapril (significant decrease in dose-adjusted AUC0-24 and Cmax) and its active metabolite enalaprilat (significant increase in dose-adjusted AUC0-24). This interaction should be given consideration in patients taking NSAIDs concomitantly with ACE-inhibitors.

Diuretics

Clinical studies, as well as post marketing observations, have shown that oxaprozin can reduce the natriuretic effect of furosemide and thiazides in some patients. This response has been attributed to inhibition of renal prostaglandin synthesis. During concomitant therapy with NSAIDs, the patient should be observed closely for signs of renal failure (see WARNINGS, Renal Effects), as well as to assure diuretic efficacy.

Lithium

Oxaprozin, like other NSAIDs, has produced an elevation of plasma lithium levels and a reduction in renal lithium clearance. The mean minimum lithium concentration increased 15% and the renal clearance was decreased by approximately 20%. These effects have been attributed to inhibition of renal prostaglandin synthesis by the nonsteroidal anti-inflammatory drug. Thus, when NSAIDs and lithium are administered concurrently, subjects should be observed carefully for signs of lithium toxicity.

Glyburide

While oxaprozin does alter the pharmacokinetics of glyburide, co-administration of oxaprozin to type II non-insulin dependent diabetic patients did not affect the area under the glucose concentration curve nor the magnitude or duration of control. However, it is advisable to monitor patients’ blood glucose in the beginning phase of glyburide and oxaprozin cotherapy.

Warfarin

The effects of warfarin and NSAIDs on gastrointestinal (GI) bleeding are synergistic, such that users of both drugs together have a risk of serious GI bleeding higher than that of users of either drug alone.

H2-Receptor Antagonists

The total body clearance of oxaprozin was reduced by 20% in subjects who concurrently received therapeutic doses of cimetidine or ranitidine; no other pharmacokinetic parameter was affected. A change of clearance of this magnitude lies within the range of normal variation and is unlikely to produce a clinically detectable difference in the outcome of therapy.

Beta- Blockers

Subjects receiving 1200 mg oxaprozin QD with 100 mg metoprolol bid exhibited statistically significant but transient increases in sitting and standing blood pressures after 14 days. Therefore, as with all NSAIDs, routine blood pressure monitoring should be considered in these patients when starting oxaprozin therapy.

Other Drugs

The co-administration of oxaprozin and antacids, acetaminophen, or conjugated estrogens resulted in no statistically significant changes in pharmacokinetic parameters in single- and/or multiple-dose studies. The interaction of oxaprozin with cardiac glycosides has not been studied.

Laboratory Test Interactions

False-positive urine immunoassay screening tests for benzodiazepines have been reported in patients taking oxaprozin. This is due to lack of specificity of the screening tests. False-positive test results may be expected for several days following discontinuation of oxaprozin therapy. Confirmatory tests, such as gas chromatography/mass spectrometry, will distinguish oxaprozin from benzodiazepines.

Carcinogenesis, Mutagenesis, Impairment of Fertility

In oncogenicity studies, oxaprozin administration for 2 years was associated with the exacerbation of liver neoplasms (hepatic adenomas and carcinomas) in male CD mice, but not in female CD mice or rats. The significance of this species-specific finding to man is unknown.

Oxaprozin did not display mutagenic potential. Results from the Ames test, forward mutation in yeast and Chinese hamster ovary (CHO) cells, DNA repair testing in CHO cells, micronucleus testing in mouse bone marrow, chromosomal aberration testing in human lymphocytes, and cell transformation testing in mouse fibroblast all showed no evidence of genetic toxicity or cell-transforming ability.

Oxaprozin administration was not associated with impairment of fertility in male and female rats at oral doses up to 200 mg/kg/day (1180 mg/m^2); the usual human dose is 17 mg/kg/day (629 mg/m^2). However, testicular degeneration was observed in beagle dogs treated with 37.5 mg/kg/day to 150 mg/kg/day (750 mg/m^2 to 3000 mg/m^2) of oxaprozin for 6 months, or 37.5 mg/kg/day for 42 days, a finding not confirmed in other species. The clinical relevance of this finding is not known.

Pregnancy

Teratogenic Effects

Pregnancy Category C:

Teratology studies with oxaprozin were performed in mice, rats, and rabbits. In mice and rats, no drug-related developmental abnormalities were observed at 50 mg/kg/day to 200 mg/kg/day of oxaprozin (225 mg/m^2 to 900 mg/m^2). However, in rabbits, infrequent malformed fetuses were observed in dams treated with 7.5 mg/kg/day to 30 mg/kg/day of oxaprozin (the usual human dosage range). Animal reproductive studies are not always predictive of human response. There are no adequate or well-controlled studies in pregnant women. Oxaprozin should be used during pregnancy only if the potential benefits justify the potential risks to the fetus.

Nonteratogenic Effects

Because of the known effects of nonsteroidal anti-inflammatory drugs on the fetal cardiovascular system (closure of ductus arteriosus), use during pregnancy (particularly late pregnancy) should be avoided.

Labor and Delivery

In rat studies with NSAIDs, as with other drugs known to inhibit prostaglandin synthesis, an increased incidence of dystocia, delayed parturition, and decreased pup survival occurred. The effects of oxaprozin on labor and delivery in pregnant women are unknown.

Nursing Mothers

It is not known whether this drug is excreted in human milk; however, oxaprozin was found in the milk of lactating rats. Because many drugs are excreted in human milk and because of the potential for serious adverse reactions in nursing infants from oxaprozin, a decision should be made whether to discontinue nursing or to discontinue the drug, taking into account the importance of the drug to the mother.

Pediatric Use

Safety and effectiveness in pediatric patients below the age of 6 years of age have not been established. The effectiveness of oxaprozin for the treatment of the signs and symptoms of juvenile rheumatoid arthritis (JRA) in pediatric patients aged 6 to 16 years is supported by evidence from adequate and well controlled studies in adult rheumatoid arthritis patients, and is based on an extrapolation of the demonstrated efficacy of oxaprozin in adults with rheumatoid arthritis and the similarity in the course of the disease and the drug’s mechanism of effect between these two patient populations. Use of oxaprozin in JRA patients 6 to 16 years of age is also supported by the following pediatric studies.

The pharmacokinetic profile and tolerability of oxaprozin were assessed in JRA patients relative to adult rheumatoid arthritis patients in a 14 day multiple dose pharmacokinetic study. Apparent clearance of unbound oxaprozin in JRA patients was reduced compared to adult rheumatoid arthritis patients, but this reduction could be accounted for by differences in body weight (see Pharmacokinetics, Special Populations, Pediatric Patients). No pharmacokinetic data are available for pediatric patients under 6 years. Adverse events were reported by approximately 45% of JRA patients versus an approximate 30% incidence of adverse events in the adult rheumatoid arthritis patient cohort. Most of the adverse events were related to the gastrointestinal tract and were mild to moderate.

In a 3 month open label study, 10 mg/kg/day to 20 mg/kg/day of oxaprozin were administered to 59 JRA patients. Adverse events were reported by 58% of JRA patients. Most of those reported were generally mild to moderate, tolerated by the patients, and did not interfere with continuing treatment. Gastrointestinal symptoms were the most frequently reported adverse effects and occurred at a higher incidence than those historically seen in controlled studies in adults. Fifty-two patients completed 3 months of treatment with a mean daily dose of 20 mg/kg. Of 30 patients who continued treatment (19 to 48 week range total treatment duration), nine (30%) experienced rash on sun-exposed areas of the skin and 5 of those discontinued treatment. Controlled clinical trials with oxaprozin in pediatric patients have not been conducted.

Geriatric Use

No adjustment of the dose of oxaprozin is necessary in the elderly for pharmacokinetic reasons, although many elderly may need to receive a reduced dose because of low body weight or disorders associated with aging. No significant differences in the pharmacokinetic profile for oxaprozin were seen in studies in the healthy elderly (see CLINICAL PHARMACOLOGY, Special Populations).

Of the total number of subjects evaluated in four placebo controlled clinical studies of oxaprozin, 39% were 65 and over, and 11% were 75 and over. No overall differences in safety or effectiveness were observed between these subjects and younger subjects, and other reported clinical experience has not identified differences in responses between the elderly and younger patients, but greater sensitivity of some older individuals cannot be ruled out.

Although selected elderly patients in controlled clinical trials tolerated oxaprozin as well as younger patients, caution should be exercised in treating the elderly, and extra care should be taken when choosing a dose. As with any NSAID, the elderly are likely to tolerate adverse reactions less well than younger patients.

Oxaprozin is substantially excreted by the kidney, and the risk of toxic reactions to oxaprozin may be greater in patients with impaired renal function. Because elderly patients are more likely to have decreased renal function, care should be taken in dose selection, and it may be useful to monitor renal function (see WARNINGS, Renal Effects).

ADVERSE REACTIONS

Adverse reaction data were derived from patients who received oxaprozin in multidose, controlled, and open-label clinical trials, and from worldwide marketing experience. Rates for events occurring in more than 1% of patients, and for most of the less common events, are based on 2,253 patients who took 1200 mg to 1800 mg oxaprozin per day in clinical trials. Of these, 1,721 were treated for at least 1 month, 971 for at least 3 months, and 366 for more than 1 year. Rates for the rarer events and for events reported from worldwide marketing experience are difficult to estimate accurately and are only listed as less than 1%.

INCIDENCE GREATER THAN 1%

In clinical trials of oxaprozin or in patients taking other NSAIDs, the following adverse reactions occurred at an incidence greater than 1%.

Cardiovascular System:edema.

Digestive System:abdominal pain/distress, anorexia, constipation, diarrhea, dyspepsia, flatulence, gastrointestinal ulcers (gastric/duodenal), gross bleeding/perforation, heartburn, liver enzyme elevations, nausea, vomiting.

Hematologic System:anemia, increased bleeding time.

Nervous System:CNS inhibition (depression, sedation, somnolence, or confusion), disturbance of sleep, dizziness, headache.

Skin and Appendages:pruritus, rash.

Special Senses:tinnitus.

Urogenital System:abnormal renal function, dysuria or frequency.

INCIDENCE LESS THAN 1%

The following adverse reactions were reported in clinical trials, from worldwide marketing experience (in italics) or in patients taking other NSAIDs.

Body as a Whole:appetite changes, death, drug hypersensitivity reactions including anaphylaxis, fever, infection, sepsis, serum sickness.

Cardiovascular System:arrhythmia, blood pressure changes, congestive heart failure, hypertension, hypotension, myocardial infarction, palpitations, tachycardia, syncope, vasculitis.

Digestive System:alteration in taste, dry mouth, eructation, esophagitis, gastritis, glossitis, hematemesis, jaundice, liver function abnormalities including hepatitis, liver failure, stomatitis, hemorrhoidal or rectal bleeding, pancreatitis.

Hematologic System:agranulocytosis, aplastic anemia, ecchymoses, eosinophilia, hemolytic anemia, lymphadenopathy, melena, pancytopenia, purpura, thrombocytopenia, leukopenia.

Metabolic System:hyperglycemia, weight changes.

Nervous System:anxiety, asthenia, coma, convulsions, dream abnormalities, drowsiness, hallucinations, insomnia, malaise, meningitis, nervousness, paresthesia, tremors, vertigo, weakness.

Respiratory System:asthma, dyspnea, pulmonary infections, pneumonia, sinusitis, symptoms of upper respiratory tract infection, respiratory depression.

Skin:alopecia, angioedema, urticaria, photosensitivity, pseudoporphyria, exfoliative dermatitis, erythema multiforme, Stevens-Johnson syndrome, sweat, toxic epidermal necrolysis (Lyell’s syndrome).

Special Senses:blurred vision, conjunctivitis, hearing decrease.

Urogenital:acute interstitial nephritis, cystitis, hematuria, increase in menstrual flow, nephrotic syndrome, oliguria/polyuria, proteinuria, renal insufficiency, acute renal failure, decreased menstrual flow.

DRUG ABUSE AND DEPENDENCE

Oxaprozin is a non-narcotic drug. Usually reliable animal studies have indicated that oxaprozin has no known addiction potential in humans.

OVERDOSAGE

No patient experienced either an accidental or intentional overdosage of oxaprozin in the clinical trials of the drug. Symptoms following acute overdose with other NSAIDs are usually limited to lethargy, drowsiness, nausea, vomiting, and epigastric pain and are generally reversible with supportive care. Gastrointestinal bleeding and coma have occurred following NSAID overdose. Hypertension, acute renal failure, and respiratory depression are rare. Anaphylactoid reactions have been reported with therapeutic ingestion of NSAIDs, and may occur following an overdose.

Patients should be managed by symptomatic and supportive care following an NSAID overdose. There are no specific antidotes. Gut decontamination may be indicated in patients seen within 4 hours of ingestion with symptoms or following a large overdose (5 to 10 times the usual dose). This should be accomplished via emesis and/or activated charcoal (60 g to 100 g in adults, 1 g/kg to 2 g/kg in children) with an osmotic cathartic. Forced diuresis, alkalization of the urine, or hemoperfusion would probably not be useful due to the high degree of protein binding of oxaprozin.

DOSAGE AND ADMINISTRATION

Carefully consider the potential benefits and risks of oxaprozin tablets and other treatment options before deciding to use oxaprozin tablets. Use the lowest effective dose for the shortest duration consistent with individual patient treatment goals (see WARNINGS).

After observing the response to initial therapy with oxaprozin tablets, the dose and frequency should be adjusted to suit an individual patient's needs.

Rheumatoid Arthritis

For relief of the signs and symptoms of rheumatoid arthritis, the usual recommended dose of oxaprozin tablets is 1200 mg (two 600 mg tablets) given orally once a day (see Individualization of Dosage).

Osteoarthritis

For relief of the signs and symptoms of osteoarthritis, the usual recommended dose of oxaprozin tablets is 1200 mg (two 600 mg tablets) given orally once a day (see Individualization of Dosage).

Juvenile Rheumatoid Arthritis

For the relief of the signs and symptoms of JRA in patients 6 to 16 years of age, the recommended dose given orally once per day should be based on body weight of the patient as given in Table 3 (see also Individualization of Dosage).

Table 3
Body Weight Range (kg) | Dose (mg)
22-31 | 600
32-54 | 900
≥55 | 1200

(see CLINICAL PHARMACOLOGY, Special Populations, Pediatric Patients)

Individualization of Dosage

As with other NSAIDs, the lowest dose should be sought for each patient. Therefore, after observing the response to initial therapy with oxaprozin tablets, the dose and frequency should be adjusted to suit an individual patient’s needs. In osteoarthritis and rheumatoid arthritis and juvenile rheumatoid arthritis, the dosage should be individualized to the lowest effective dose of oxaprozin tablets to minimize adverse effects. The maximum recommended total daily dose of oxaprozin tablets in adults is 1800 mg (26 mg/kg, whichever is lower) in divided doses. In children, doses greater than 1200 mg have not been studied.

Patients of low body weight should initiate therapy with 600 mg once daily. Patients with severe renal impairment or on dialysis should also initiate therapy with 600 mg once daily. If there is insufficient relief of symptoms in such patients, the dose may be cautiously increased to 1200 mg, but only with close monitoring (see CLINICAL PHARMACOLOGY, Special Populations).

In adults, in cases where a quick onset of action is important, the pharmacokinetics of oxaprozin allows therapy to be started with a one-time loading dose of 1200 mg to 1800 mg (not to exceed 26 mg/kg). Doses larger than 1200 mg/day on a chronic basis should be reserved for patients who weigh more than 50 kg, have normal renal and hepatic function, are at low risk of peptic ulcer, and whose severity of disease justifies maximal therapy. Physicians should ensure that patients are tolerating doses in the 600 mg/day to 1200 mg/day range without gastroenterologic, renal, hepatic, or dermatologic adverse effects before advancing to the larger doses. Most patients will tolerate once-a-day dosing with oxaprozin, although divided doses may be tried in patients unable to tolerate single doses.

Safety and Handling

Oxaprozin is supplied as a solid dosage form in closed containers, is not known to produce contact dermatitis, and poses no known risk to healthcare workers. It may be disposed of in accordance with applicable local regulations governing the disposal of pharmaceuticals.

HOW SUPPLIED

Oxaprozin tablets USP for oral administration are available as:

600 mg: White, capsule-shaped, film-coated, debossed with “E141” on one side and bisected on the other, and supplied as:

NDC 66336-0722-60 bottles of 60

Store at 20° to 25°C (68° to 77°F) [see USP Controlled Room Temperature]. Keep bottles tightly closed.

Dispense in a tight, light-resistant container as defined in the USP with a child-resistant closure, as required.

Medication Guide for Non-Steroidal Anti-Inflammatory Drugs (NSAIDs)

(See the end of this Medication Guide for a list of prescription NSAID medicines.)

What is the most important information I should know about medicines called Non-Steroidal Anti-Inflammatory Drugs (NSAIDs)?

NSAID medicines may increase the chance of a heart attack or stroke that can lead to death. This chance increases:

- with longer use of NSAID medicines
- in people who have heart disease

NSAID medicines should never be used right before or after a heart surgery called a “coronary artery bypass graft (CABG).”

NSAID medicines can cause ulcers and bleeding in the stomach and intestines at any time during treatment. Ulcers and bleeding:

- can happen without warning symptoms
- may cause death

The chance of a person getting an ulcer or bleeding increases with:

- taking medicines called “corticosteroids” and “anticoagulants”
- longer use
- smoking
- drinking alcohol
- older age
- having poor health

NSAID medicines should only be used:

- exactly as prescribed
- at the lowest dose possible for your treatment
- for the shortest time needed

What are Non-Steroidal Anti-Inflammatory Drugs (NSAIDs)?

NSAID medicines are used to treat pain and redness, swelling, and heat (inflammation) from medical conditions such as:

- different types of arthritis
- menstrual cramps and other types of short-term pain

Who should not take a Non-Steroidal Anti-Inflammatory Drug (NSAID)?

Do not take an NSAID medicine:

- if you had an asthma attack, hives, or other allergic reaction with aspirin or any other NSAID medicine
- for pain right before or after heart bypass surgery

Tell your healthcare provider:

- about all of your medical conditions.
- about all of the medicines you take. NSAIDs and some other medicines can interact with each other and cause serious side effects. Keep a list of your medicines to show to your healthcare provider and pharmacist.
- if you are pregnant. NSAID medicines should not be used by pregnant women late in their pregnancy.
- if you are breastfeeding. Talk to your doctor.

What are the possible side effects of Non-Steroidal Anti-Inflammatory Drugs (NSAIDs)?

Serious side effects include:

- heart attack

- stroke

- high blood pressure

- heart failure from body swelling (fluid retention)

- kidney problems including kidney failure

- bleeding and ulcers in the stomach and intestine

- low red blood cells (anemia)

- life-threatening skin reactions

- life-threatening allergic reactions

- liver problems including liver failure

- asthma attacks in people who have asthma

Other side effects include:

- stomach pain

- constipation

- diarrhea

- gas

- heartburn

- nausea

- vomiting

- dizziness

Get emergency help right away if you have any of the following symptoms:

- shortness of breath or trouble breathing
- chest pain
- weakness in one part or side of your body
- slurred speech
- swelling of the face or throat

Stop your NSAID medicine and call your healthcare provider right away if you have any of the following symptoms:

- nausea
- more tired or weaker than usual
- itching
- your skin or eyes look yellow
- stomach pain
- flu-like symptoms
- vomit blood
- there is blood in your bowel movement or it is black and sticky like tar
- skin rash or blisters with fever
- unusual weight gain
- swelling of the arms and legs, hands and feet

These are not all the side effects with NSAID medicines. Talk to your healthcare provider or pharmacist for more information about NSAID medicines.

Other information about Non-Steroidal Anti-Inflammatory Drugs (NSAIDs)

- Aspirin is an NSAID medicine but it does not increase the chance of a heart attack. Aspirin can cause bleeding in the brain, stomach, and intestines. Aspirin can also cause ulcers in the stomach and intestines.
- Some of these NSAID medicines are sold in lower doses without a prescription (over–the–counter). Talk to your healthcare provider before using over–the–counter NSAIDs for more than 10 days.

NSAID medicines that need a prescription

Generic Name | Tradename
Celecoxib | Celebrex
Diclofenac | Cataflam, Voltaren, Arthrotec (combined with misoprostol)
Diflunisal | Dolobid
Etodolac | Lodine, Lodine XL
Fenoprofen | Nalfon, Nalfon 200
Flurbiprofen | Ansaid
Ibuprofen | Motrin, Tab-Profen, Vicoprofen [Vicoprofen contains the same dose of ibuprofen as over-the-counter (OTC) NSAIDs, and is usually used for less than 10 days to treat pain. The OTC NSAID label warns that long term continuous use may increase the risk of heart attack or stroke.] (combined with hydrocodone), Combunox (combined with oxycodone)
Indomethacin | Indocin, Indocin SR, Indo-Lemmon, Indomethagan
Ketoprofen | Oruvail
Ketorolac | Toradol
Mefenamic Acid | Ponstel
Meloxicam | Mobic
Nabumetone | Relafen
Naproxen | Naprosyn, Anaprox, Anaprox DS, EC-Naproxyn, Naprelan, Naprapac (copackaged with lansoprazole)
Oxaprozin | Daypro
Piroxicam | Feldene
Sulindac | Clinoril
Tolmetin | Tolectin, Tolectin DS, Tolectin 600

This Medication Guide has been approved by the U.S. Food and Drug Administration.

Call your doctor for medical advice about side effects. You may report side effects to FDA at 1-800-FDA-1088.

Sandoz Inc.

Princeton, NJ 08540

46075012

Rev. 03/13

MF0141REV03/13

600 mg - Label

NDC 66336-0722-XX

NDC 66336-0722-60

Oxaprozin Tablets USP

600 mg

PHARMACIST: Please dispense with Medication Guide provided separately.

Rx only